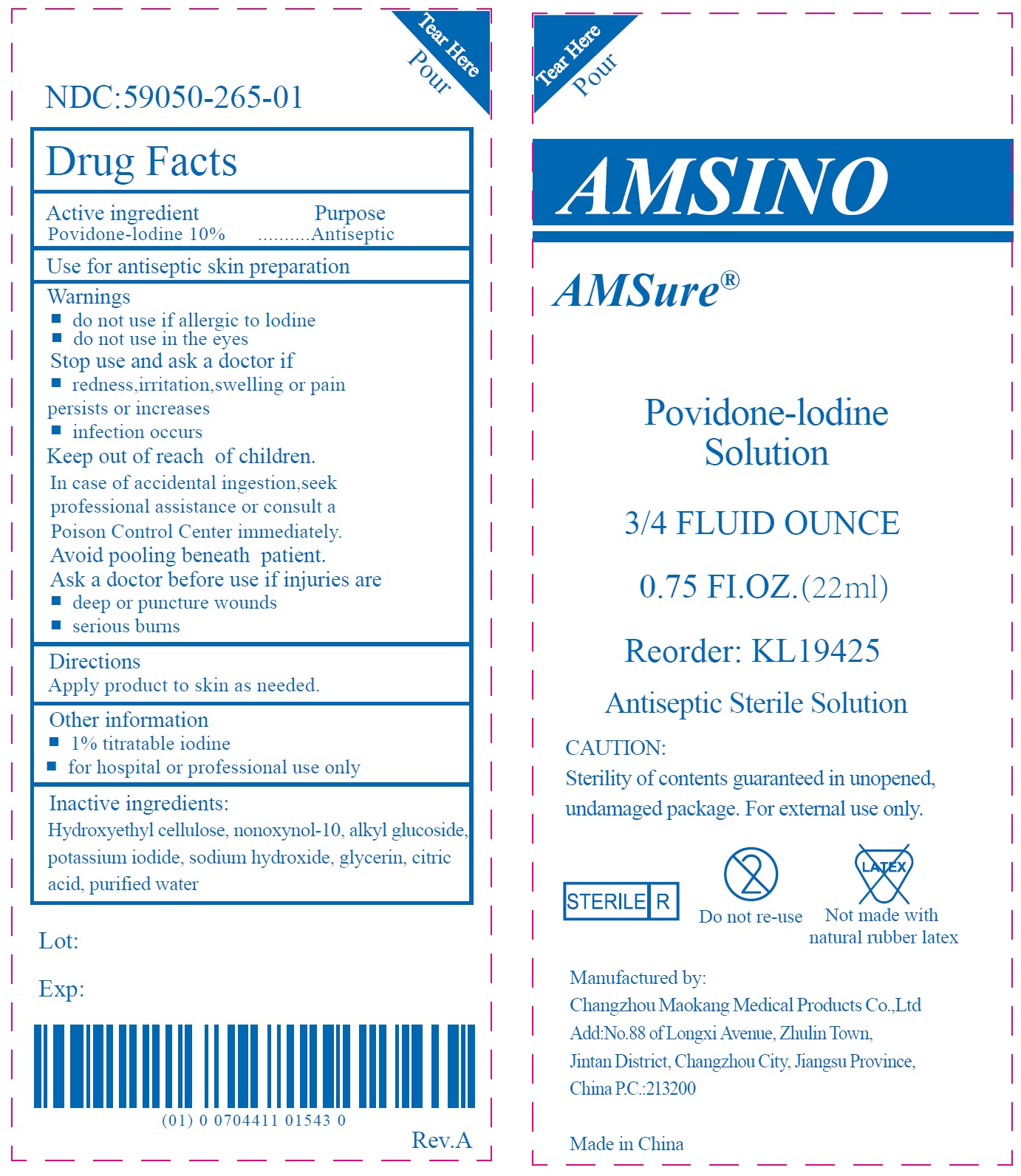 DRUG LABEL: Amsino 10 Povidone-Iodine Solution 3 4 Fluid Ounce
NDC: 59050-265 | Form: LIQUID
Manufacturer: Changzhou Maokang Medical Products Co., Ltd
Category: otc | Type: HUMAN OTC DRUG LABEL
Date: 20241121

ACTIVE INGREDIENTS: POVIDONE-IODINE 100 mg/1 mL
INACTIVE INGREDIENTS: HYDROXYETHYL CELLULOSE, UNSPECIFIED; NONOXYNOL-10; POTASSIUM IODIDE; SODIUM HYDROXIDE; GLYCERIN; CITRIC ACID MONOHYDRATE; WATER

Amsino 10% Povidone-Iodine Solution 3/4 Fluid Ounce

Active ingredient

Povidone-lodine 10%

Purpose

Antiseptic

Use

for antiseptic skin preparation

Warnings

do not use

- if allergic to lodine
- do not use in the eyes

Stop use and ask a doctor if

- redness,irritation,swelling or pain persists or increases
- infection occurs

Keep out of reach of children.

In case of accidental ingestion,seek professional assistance or consult a Poison Control Center immediately. Avoid pooling beneath patient.

Ask a doctor before use

if injuries are

- deep or puncture wounds
- serious burns

Directions

Apply product to skin as needed.

Other information

- 1% titratable iodine
- for hospital or professional use only

Inactive ingredients:

Hydroxyethyl cellulose, nonoxynol-10, alkyl glucoside, potassium iodide, sodium hydroxide, glycerin, citric acid, purified water